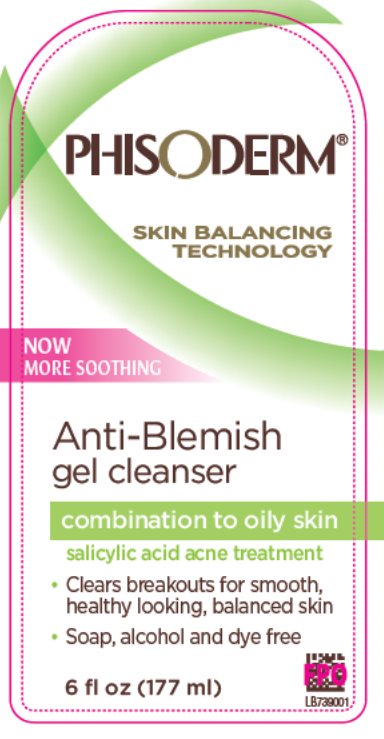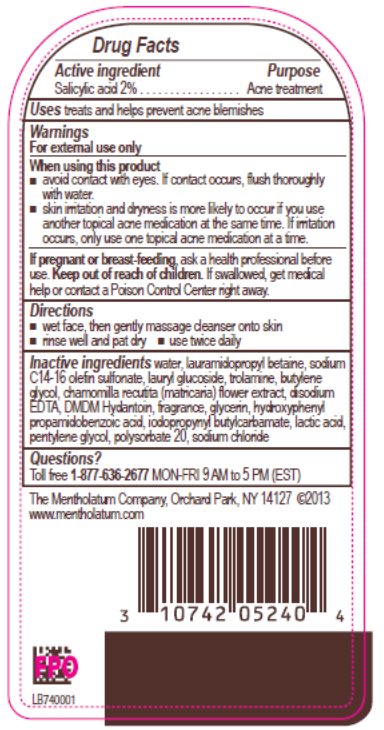 DRUG LABEL: Phisoderm Anti-Blemish Gel Cleanser
NDC: 10742-8417 | Form: GEL
Manufacturer: The Mentholatum Company
Category: otc | Type: HUMAN OTC DRUG LABEL
Date: 20241217

ACTIVE INGREDIENTS: SALICYLIC ACID 20 mg/1 g
INACTIVE INGREDIENTS: WATER; LAURAMIDOPROPYL BETAINE; SODIUM C14-16 OLEFIN SULFONATE; LAURYL GLUCOSIDE; TROLAMINE; BUTYLENE GLYCOL; CHAMOMILE; EDETATE DISODIUM; DMDM HYDANTOIN; GLYCERIN; HYDROXYPHENYL PROPAMIDOBENZOIC ACID; IODOPROPYNYL BUTYLCARBAMATE; LACTIC ACID, UNSPECIFIED FORM; PENTYLENE GLYCOL; POLYSORBATE 20; SODIUM CHLORIDE

Drug Facts - pHisoderm Anti-Blemish Gel Cleanser

Active ingredient

Salicylic acid 2%

Purpose

Acne treatment

Uses

treats and helps prevent acne blemishes

Warnings

For external use only

When using this product

- avoid contact with the eyes. If contact occurs, flush thoroughly with water.
- skin irritation and dryness is more likely to occur if you use another topical acne medication at the same time. If irritation occurs, only use one topical acne medication at a time.

If pregnant or breast-feeding

ask a health professional before use.

Keep Out of Reach of Children

If swallowed, get medical help or contact a Poison Control Center right away.

Directions

- wet face, then gently massage onto skin
- Rinse well and pat dry
- use twice daily

Inactive ingredients

water, lauramidopropyl betaine, sodium C14-16 olefin sulfonate, lauryl glucoside, trolamine, butylene glycol, chamomilla recutita (matricaria) flower extract, disodium EDTA, DMDM hydantoin, fragrance, glycerin, hydroxyphenyl propamidobenzoic acid, iodopropynyl butylcarbamate, lactic acid, pentylene glycol, polysorbate 20, sodium chloride

Questions?

Toll free 1-877-636-2677 MON-FRI 9 AM-5 PM (EST)